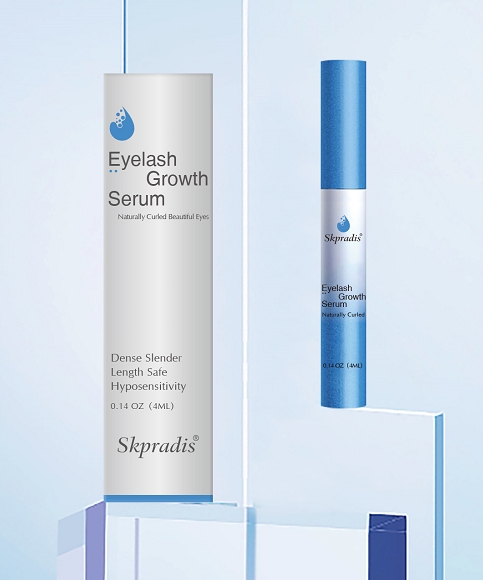 DRUG LABEL: Skpradis Eyelash Conditioner
NDC: 84507-035 | Form: LIQUID
Manufacturer: Guangdong Miaolian Cosmetics Co., Ltd.
Category: otc | Type: HUMAN OTC DRUG LABEL
Date: 20250331

ACTIVE INGREDIENTS: MYRISTOYL PENTAPEPTIDE-4 0.01 mg/100 mL
INACTIVE INGREDIENTS: PENTYLENE GLYCOL; PAEONIA ALBIFLORA FLOWER; GLYCERYL CAPRYLATE; AQUA; MALTOOLIGOSYL GLUCOSIDE; HYDROXYETHYLCELLULOSE; CAPRYLHYDROXAMIC ACID; EDETATE DISODIUM; HYDROGENATED STARCH HYDROLYSATE; METHYLPROPANEDIOL; HYDROXYACETOPHENONE; 1,2-HEXANEDIOL; GLYCERIN; BUTYLENE GLYCOL

WARNINGS

Risk InformationFor external use only
Mention de risquesPour usage externe seulement
Do not use on damaged or broken skin.
Ne pas utiliser sur la peau endommagée ou avec des lésions
If rash occurs, discontinue use and consult a health care practitioner.
En présence d'une éruption cutanée, cesser l'utilisation et consulter un praticien de soins de santé
When using this product keep out of eyes. Rinse with water to remove.
Eviter tout contact avec les yeux. Rincer a l'eau le cas échéant
Keep out of reach of children. If swallowed, get medical help or contact a Poison Control Center right away.
Tenir hors de portée des enfants
En cas d'ingestion, consulter un médecin ou appeler un centre antipoison immédiatement.

PURPOSE

Eyelash Growth

Keep out of reach of children. If swallowed, get medical help or contact a Poison Control Center right away.

DOSAGE AND ADMINISTRATION

shake well before use.Wash and thoroughly dry the affectedarea. Apply 1-2 drops and gently rubinto affected area three times per day.

INACTIVE INGREDIENT

AQUA
GLYCERIN
BUTYLENE GLYCOL
PENTYLENE GLYCOL
MALTOOLIGOSYL GLUCOSIDE
METHYLPROPANEDIOL
HYDROXYETHYLCELLULOSE
HYDROGENATED STARCH HYDROLYSATE
HYDROXYACETOPHENONE
CAPRYLHYDROXAMIC ACID
PAEONIA ALBIFLORA ROOT EXTRACT
DISODIUM EDTA
1,2-HEXANEDIOL
GLYCERYL CAPRYLATE

ACTIVE INGREDIENT

MYRISTOYL PENTAPEPTIDE-4 -----0.01%

INDICATIONS AND USAGE

With regular use of eyelash growth serum, you can experience a dramatic increase in the length and thickness of your lashes and brows! Lashes grow significantly within two weeks. Each tube promotes new lash growth and strengthens existing lashes for bold, eye-catching eyes.